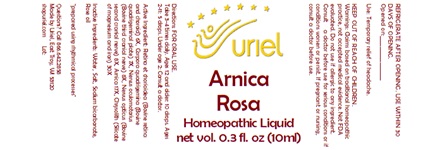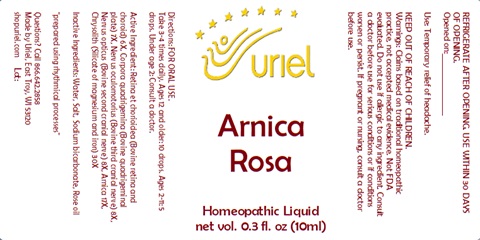 DRUG LABEL: Arnica Rosa
NDC: 48951-1373 | Form: LIQUID
Manufacturer: Uriel Pharmacy Inc.
Category: homeopathic | Type: HUMAN OTC DRUG LABEL
Date: 20240327

ACTIVE INGREDIENTS: BOS TAURUS BRAIN 7 [hp_X]/1 mL; ARNICA MONTANA 17 [hp_X]/1 mL; BOS TAURUS NERVE 8 [hp_X]/1 mL; BOS TAURUS EYE 6 [hp_X]/1 mL; SILICON DIOXIDE 30 [hp_X]/1 mL
INACTIVE INGREDIENTS: ROSE OIL; SODIUM CHLORIDE; WATER; SODIUM BICARBONATE

Arnica Rosa

INDICATIONS AND USAGE

Directions: FOR ORAL USE.

DOSAGE AND ADMINISTRATION

Take 3-4 times daily. Ages 12 and older: 10 drops. Ages 2-11: 5 drops. Under age 2: Consult a doctor.

Active Ingredient: Retina et chorioidea (Bovine retina and choroid) 6X, Corpara quadrigemina (Bovine quadrigeminal plate) 7X, Nervus oculomotorius (Bovine third cranial nerve) 8X, Nervus opticus (Bovine second cranial nerve) 8X Arnica 17X, Chrysolith (Silicate of magnesium and iron) 30X

Inactive Ingredients: Water, Salt, Sodium bicarbonate, Rose oil

prepared using rhythmical processes

PURPOSE

Use: Temporary relief of headache.

KEEP OUT OF REACH OF CHILDREN.

KEEP OUT OF REACH OF CHILDREN.
Warnings: Claims based on traditional homeopathic practice, not accepted medical evidence. Not FDA evaluated. Do not use if allergic to any ingredient. Consult a doctor before use for serious conditions or if conditions worsen or persist. If pregnant or nursing, consult a doctor before use. Do not use if safety seal is broken or missing.

REFRIGERATE AFTER OPENING. USE WITHIN 30 DAYS OF OPENING.
Opened on:_________________

Questions? Call 866.642.2858
Made by Uriel, East Troy, WI 53120
shopuriel.com Lot: